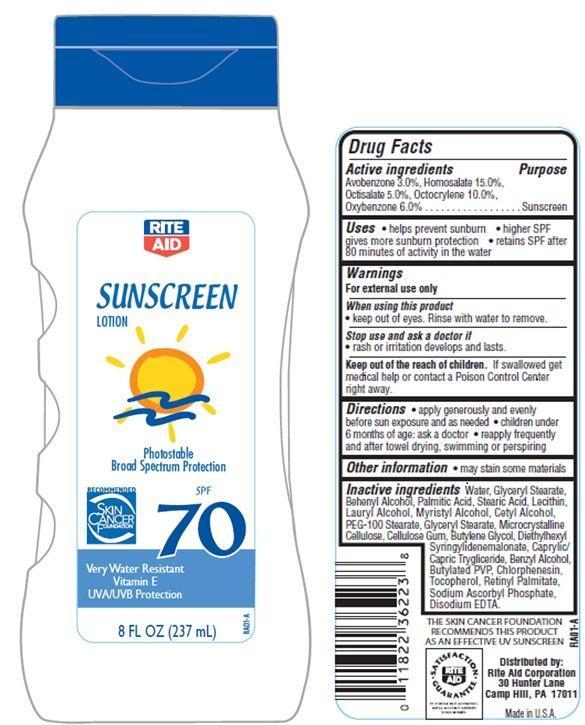 DRUG LABEL: Rite Aid Sunscreen
NDC: 11822-9011 | Form: LOTION
Manufacturer: RITE AID CORPORATION
Category: otc | Type: HUMAN OTC DRUG LABEL
Date: 20121204

ACTIVE INGREDIENTS: AVOBENZONE 3 g/100 g; HOMOSALATE 15 g/100 g; OCTISALATE 5 g/100 g; OCTOCRYLENE 10 g/100 g; OXYBENZONE 6 g/100 g
INACTIVE INGREDIENTS: WATER; DOCOSANOL; PALMITIC ACID; PEG-100 STEARATE; GLYCERYL MONOSTEARATE; STEARIC ACID; EDETATE DISODIUM; LAURYL ALCOHOL; MYRISTYL ALCOHOL; CHLORPHENESIN; CETYL ALCOHOL; CELLULOSE, MICROCRYSTALLINE; CARBOXYMETHYLCELLULOSE SODIUM; BUTYLENE GLYCOL; DIETHYLHEXYL SYRINGYLIDENEMALONATE; TRICAPRIN; BENZYL ALCOHOL; TOCOPHEROL; VITAMIN A PALMITATE; SODIUM ASCORBYL PHOSPHATE

Drug Facts

Active ingredients

Avobenzone 3.0 %

Homosalate 15.0%

Octisalate 5.0%

Octocrylene 10.0%

Oxybenzone 6.0%

Purpose

Sunscreen

Uses

- helps prevent sunburn
- higher SPF gives more sunburn protection
- retains SPF after 80 minutes of activity in the water

Warnings

For external use only

When using this product

- keep out of eyes. Rinse with water to remove.

Stop use and ask a doctor if

- rash or irritation develops and lasts.

Keep out of reach of children.

If swallowed, get medical help or contact a Poison Control Center right away.

Directions

- apply generously and evenly before sun exposure and as needed
- children under 6 months of age:ask a doctor
- reapply frequently and after towel drying, swimming or perspiring.

Other Information

- may stain some materials

Inactive Ingredients

Water, Glyceryl Stearate, Microcrystalline Cellulose, Butylene Glycol, PEG-100 Stearate, Acrylates/C12-22 Alkyl Methacrylate Copolymer, Benzyl Alcohol, Diethylhexyl Syringylidenemalonate, Behenyl Alcohol, Butylated PVP, Palmitic Acid, Stearic Acid, C12-16 Alcohols, Cellulose Gum, Caprylic/Capric Triglyceride, Lecithin, Retinyl Palmitate, Tocopherol, Sodium Ascorbyl Phosphate, Disodium EDTA, Chlorphenesin.

Principal Display Panel

RITE AID
SUNSCREEN LOTION
Photostable
Broad Spectrum Protection
RECOMMENDED
SKIN CANCER FOUNDATION
SPF 70
Very Water Resistant
Vitamin E
UVA/UVB Protection
8 FL OZ (237 mL)